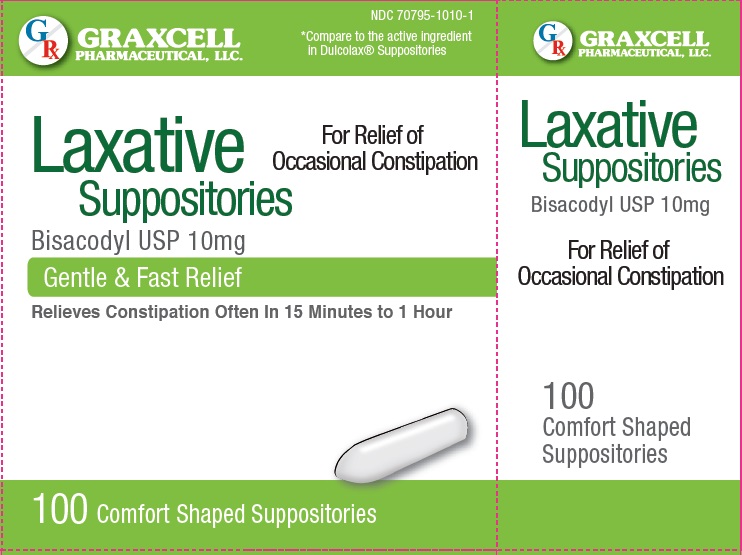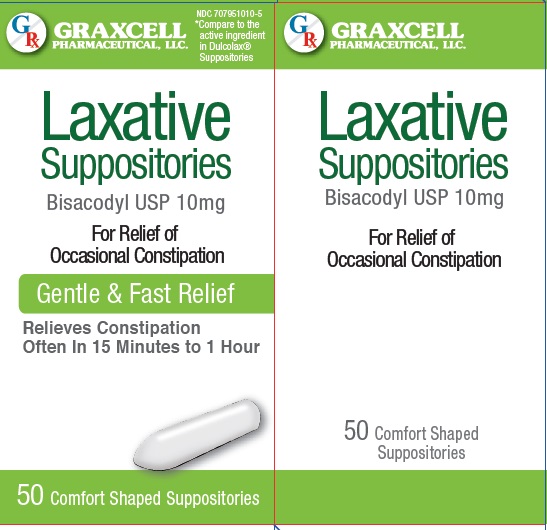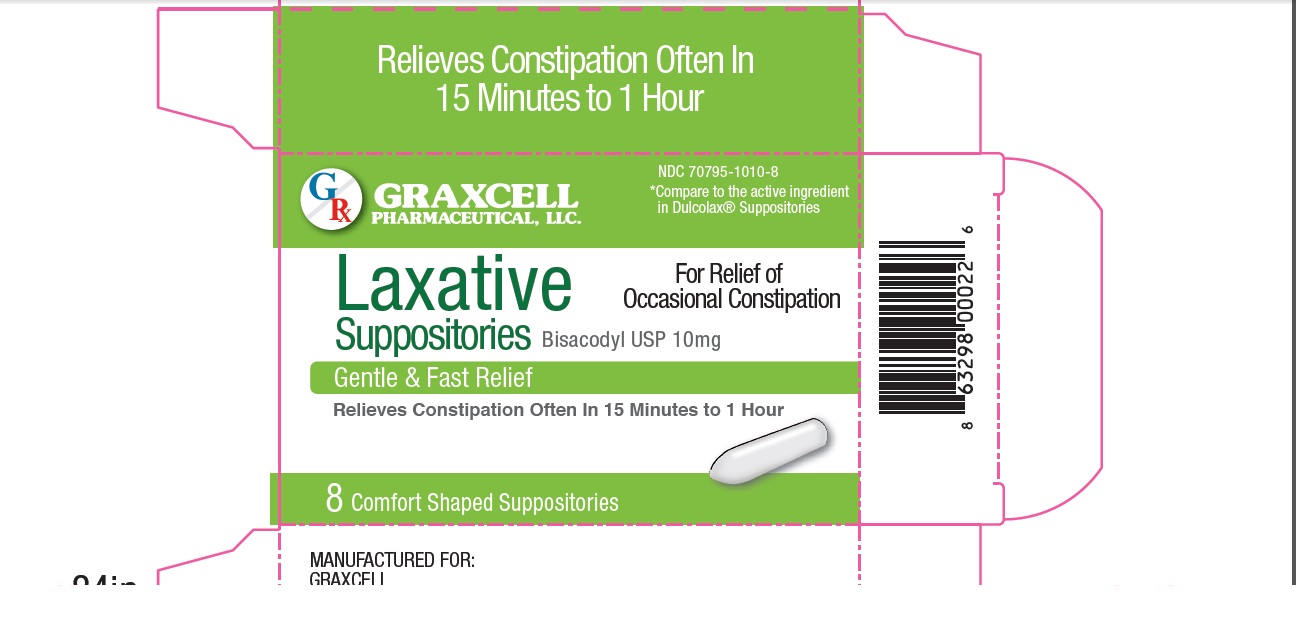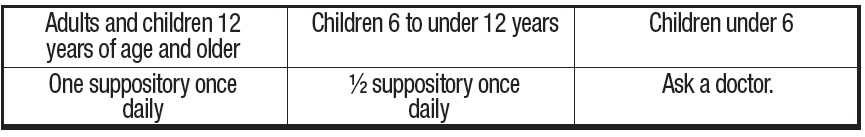 DRUG LABEL: LAXATIVE
NDC: 70795-1010 | Form: SUPPOSITORY
Manufacturer: GRAXCELL PHARMACEUTICAL, LLC
Category: otc | Type: HUMAN OTC DRUG LABEL
Date: 20251225

ACTIVE INGREDIENTS: BISACODYL 10 mg/1 1
INACTIVE INGREDIENTS: FAT, HARD

LAXATIVE SUPPOSITORIES, 70795-1010

Active Ingredient (in each suppository)

Bisacodyl, 10 mg

Purpose

Stimulant Laxative

Uses

- For relief of occasional constipation
- This product generally produces bowel movement in 15 minutes to 1 hour

Warnings

For rectal use only. May cause abdominal discomfort, faintness, rectal burning, and mild cramps.

Do not use

- more than once per day
- for a period longer than one week unless directed by a doctor
- laxative products when abdominal pain, nausea, or vomitting are present unless directed by a doctor
- if sealed film around the suppository is torn, damaged, or open.

Ask a doctor

- before use if you have noticed a sudden change in bowel habits that persist over a period of two weeks
- if you are pregnant or nursing a baby

Stop use and ask a doctor

if you have rectal bleeding or fail to have a bowel movement after using a laxative. This may indicate a serious condition.

Keep out of reach of children

If swallowed, get medical help or contact a Poison Control Center right away.

Directions

- Detach one suppository from the strip and remove from foil
- Carefully insert one supoository well into the rectum
- Do not use more than once per day

Other information

store below 30° C (86° F)

Inactive ingredient

hydrogenated vegetable oil